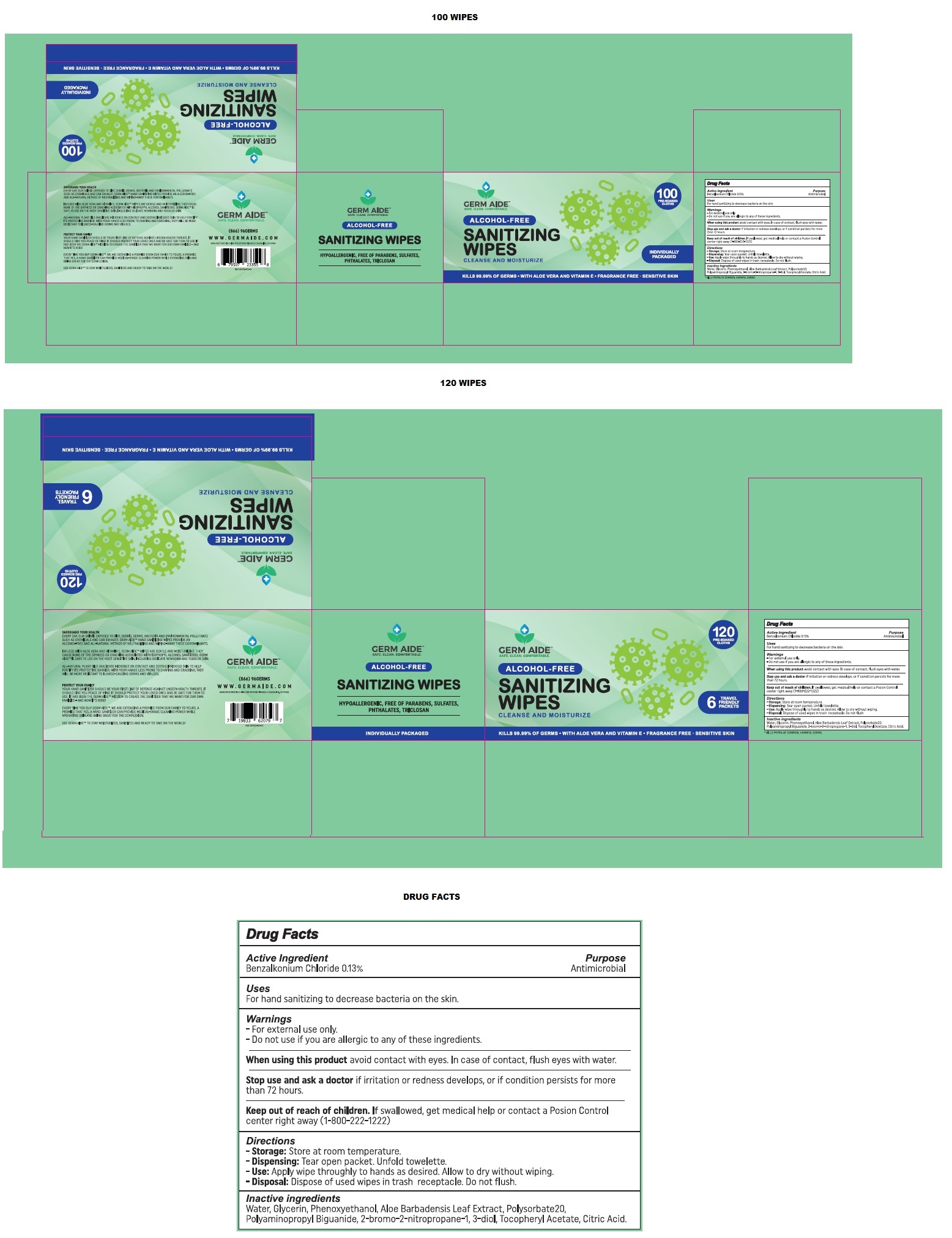 DRUG LABEL: Germ Aide ALCOHOL-FREE SANITIZING WIPES
NDC: 80952-101 | Form: CLOTH
Manufacturer: Beyond Pinnacle
Category: otc | Type: HUMAN OTC DRUG LABEL
Date: 20201207

ACTIVE INGREDIENTS: BENZALKONIUM CHLORIDE 1.3 mg/1 mL
INACTIVE INGREDIENTS: WATER; GLYCERIN; PHENOXYETHANOL; ALOE VERA LEAF; POLYSORBATE 20; POLYAMINOPROPYL BIGUANIDE; BRONOPOL; .ALPHA.-TOCOPHEROL ACETATE; CITRIC ACID MONOHYDRATE

GERM AIDE™ALCOHOL-FREE SANITIZING WIPES

Active Ingredient

Benzalkonium Chloride 0.13%

Purpose

Antimicrobial

Uses

For hand sanitizing to decrease bacteria on the skin.

Warnings

- For external use only.

- Do not use if you are allergic to any of these ingredients.

When using this product avoid contact with eyes. In case of contact, flush eyes with water.

Stop use and ask a doctor if irritation or redness develops, or if conditions persists for more than 72 hours.

Keep out of reach of children. If swallowed, get medical help or contact a Poison Control center right away (1-800-222-1222)

Directions

- Storage: Store at room temperature.

- Dispensing: Tear open packet. Unfold towelette.

- Use: Apply wipe thoroughly to hands as desired. Allow to dry without wiping.

- Disposal: Dispose of used wipes in trash receptacle. Do not flush.

Inactive ingredients

Water, Glycerin, Phenoxyethanol, Aloe Barbadensis Leaf Extract, Polysorbate 20, Polyaminopropyl Biguanide, 2-bromo-2-nitropropane-1, 3-diol, Tocopheryl Acetate, Citric Acid.

GERM AIDE™

SAFE. CLEAN. COMFORTABLE.

100 PRE-SOAKED CLOTHS

CLEANSE AND MOISTURIZE

INDIVIDUALLY PACKAGED

KILLS 99.99% OF COMMON, HARMFUL GERMS • WITH ALOE VERA AND VITAMIN E • FRAGRANCE FREE • SENSITIVE SKIN

SAFEGUARD YOUR HEALTH

EVERY DAY, OUR SKIN IS EXPOSED TO DIRT, DEBRIS, GERMS, BACTERIA AND ENVIRONMENTAL POLLUTANTS SUCH AS CHEMICALS AND CAR EXHAUST. GERM AIDE™ HAND SANITIZING WIPES PROVIDE AN ALCOHOL-FREE AND ALL-NATURAL METHOD OF NEUTRALIZING AND WIPING-AWAY THESE CONTAMINANTS.

INFUSED WITH ALOE VERA AND VITAMIN E, GERM AIDE™ WIPES ARE GENTLE AND MOISTURIZING. THEY CAUSE NONE OF THE DRYNESS OR CRACKING ASSOCIATED WITH ISOPROPYL ALCOHOL SANITIZERS. GERM AIDE™ IS SAFE TO USE ON THE MOST SENSITIVE SKIN, INCLUDING DELICATE NEWBORN AND TODDLER SKIN.

ALL-NATURAL PLANT OILS ERADICATE MICROBES ON CONTACT AND SOOTHE IRRITATED SKIN TO HELP FORTIFY ITS PROTECTIVE BARRIER. WITH YOUR HANDS LESS PRONE TO CHAFING AND CRACKING, THEY WILL BE MORE RESISTANT TO ILLNESS-CAUSING GERMS AND VIRUSES.

PROTECT YOUR FAMILY

YOUR HAND SANITIZER SHOULD BE YOUR FIRST LINE OF DEFENSE AGAINST UNSEEN HEALTH THREATS. IT SHOULD GIVE YOU PEACE OF MIND. IT SHOULD PROTECT YOUR LOVED ONES AND BE SAFE FOR THEM TO USE. IT HAS BEEN THE GERM AID™ MISSION TO CREATE THE SANITIZER THAT WE WANT FOR OUR OWN FAMILIES - AND NOW IT'S HERE!

EVERY TIME YOU BUY GERM AIDE™, WE ARE EXTENDING A PROMISE FROM OUR FAMILY TO YOURS. A PROMISE THAT YES, A HAND SANITIZER CAN PROVIDE MEDICAL-GRADE CLEANING POWER WHILE HYDRATING SKIN AND BEING GREAT FOR THE COMPLEXION.

USE GERM AIDE™ TO STAY MOISTURIZED, SANITIZED AND READY TO TAKE ON THE WORLD!

(866) 96GERMS

WWW.GERMAIDE.COM

MANUFACTURED IN CHINA FOR BEYOND PINNACLE SAUSALITO, CA 94965

HYPOALLERGENIC, FREE OF PARABENS, SULFATES, PHTHALATES, TRICLOSAN